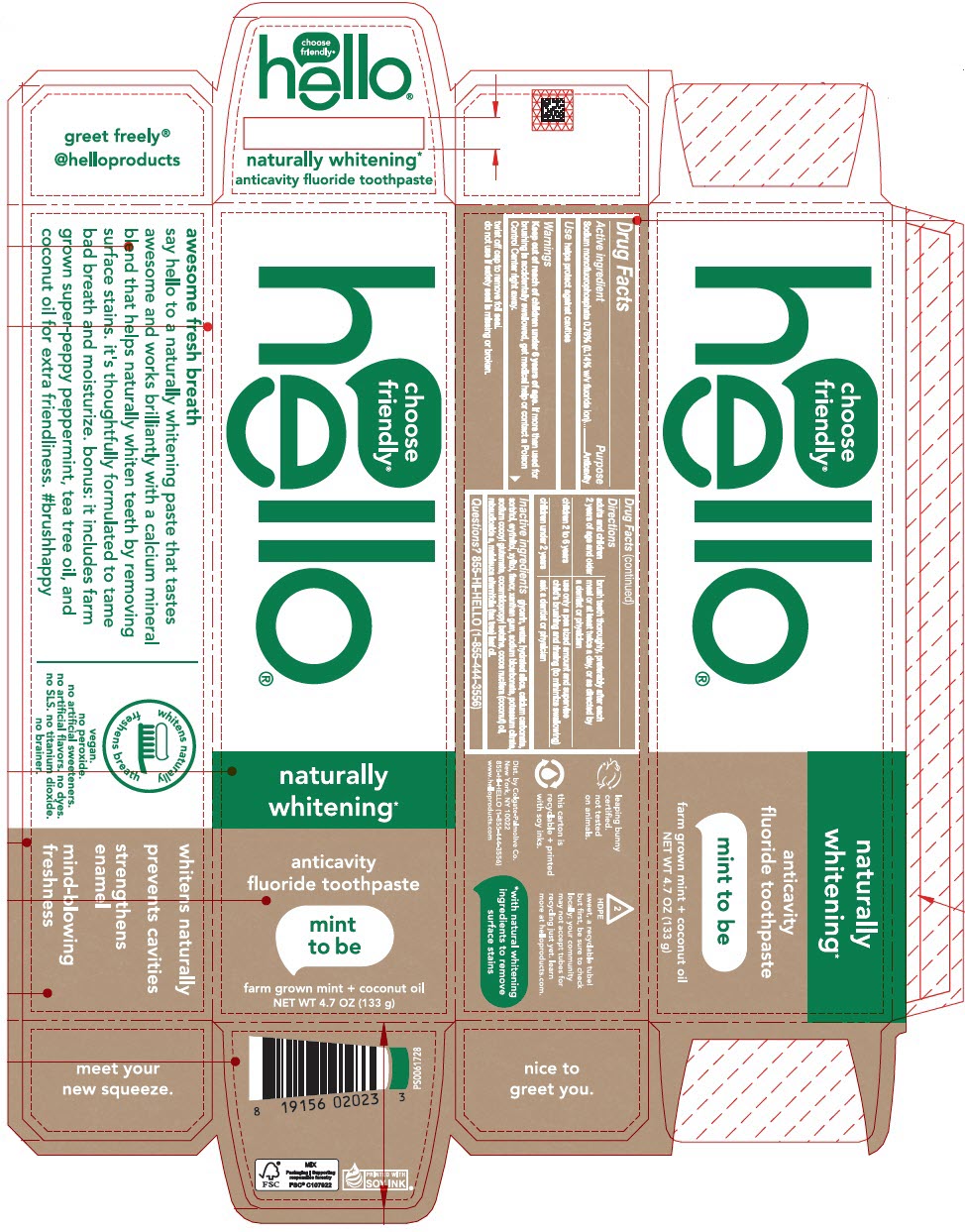 DRUG LABEL: Hello Naturally Whitening
NDC: 35000-682 | Form: PASTE, DENTIFRICE
Manufacturer: COLGATE PALMOLIVE COMPANY
Category: otc | Type: HUMAN OTC DRUG LABEL
Date: 20251111

ACTIVE INGREDIENTS: SODIUM MONOFLUOROPHOSPHATE 1.1 mg/1 g
INACTIVE INGREDIENTS: GLYCERIN; WATER; HYDRATED SILICA; CALCIUM CARBONATE; SORBITOL; ERYTHRITOL; XYLITOL; XANTHAN GUM; SODIUM BICARBONATE; POTASSIUM CITRATE; SODIUM COCOYL GLUTAMATE; COCAMIDOPROPYL BETAINE; COCONUT OIL; REBAUDIOSIDE A; TEA TREE OIL

Hello® Naturally Whitening

Drug Facts

Active ingredient

Sodium monofluorophosphate 0.76% (0.14% w/v fluoride ion)

Purpose

Anticavity

Use

helps protect against cavities

Warnings

Keep out of reach of children under 6 years of age. If more than used for brushing is accidentally swallowed, get medical help or contact a Poison Control Center right away.

twist off cap to remove foil seal.

do not use if safety seal is missing or broken.

Directions

adults and children 2 years of age and older | brush teeth thoroughly, preferably after each meal or at least twice a day, or as directed by a dentist or physician
children 2 to 6 years | use only a pea sized amount and supervise child's brushing and rinsing (to minimize swallowing)
children under 2 years | ask a dentist or physician

Inactive ingredients

glycerin, water, hydrated silica, calcium carbonate, sorbitol, erythritol, xylitol, flavor, xanthan gum, sodium bicarbonate, potassium citrate, sodium cocoyl glutamate, cocamidopropyl betaine, cocos nucifera (coconut) oil, rebaudioside a, melaleuca alternifolia (tea tree) leaf oil.

Questions?

855-HI-HELLO (1-855-444-3556)

Dist. by Colgate-Palmolive Co.
New York, NY 10022

PRINCIPAL DISPLAY PANEL - 133 g Tube Carton

choose
friendly®
hello®

naturally
whitening*

anticavity
fluoride toothpaste

mint
to be

farm grown mint + coconut oil
NET WT 4.7 OZ (133 g)